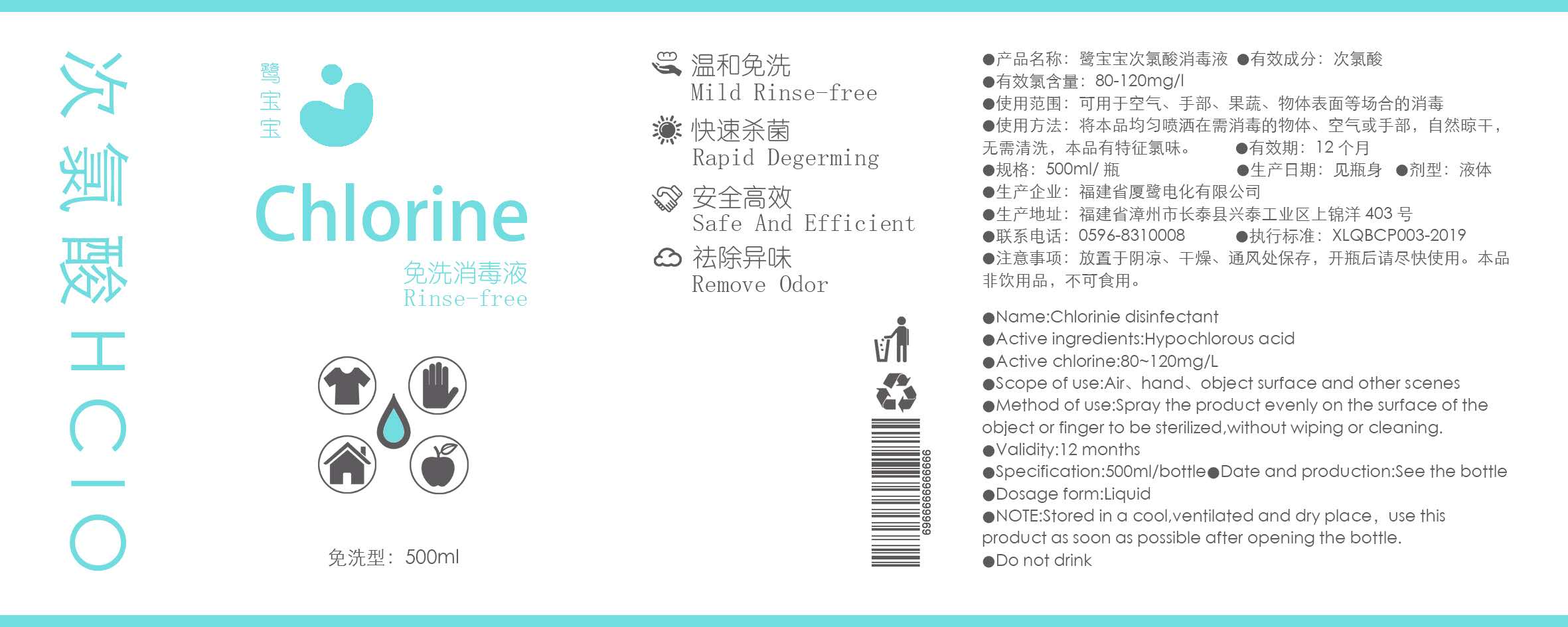 DRUG LABEL: Chlorinie disinfectant
NDC: 75434-005 | Form: LIQUID
Manufacturer: Fujian Xialu Electrochemical Co., Ltd.
Category: otc | Type: HUMAN OTC DRUG LABEL
Date: 20200416

ACTIVE INGREDIENTS: HYPOCHLOROUS ACID 12 mg/100 mL
INACTIVE INGREDIENTS: WATER

Active Ingredient(s)

HYPOCHLOROUS ACID 12%

Purpose

Antiseptic

Use

AIR,HAND,OBJECT SURFACE AND OTHER SCENES.

Warnings

STORED IN A COOL,VENTILATED AND DRY PLACE ,USE THIS PRODUCT AS SOON AS POSSIBLE AFTER OPENING THE BOTTLE.DO NOT DRINK.

Do not use

Not for human body

When using this product keep out of eyes, ears, and mouth. In case of contact with eyes, rinse eyes thoroughly with water.
Stop use and ask a doctor if irritation or rash occurs. These may be signs of a serious condition.
Keep out of reach of children. If swallowed, get medical help or contact a Poison Control Center right away.

Stop use and ask a doctor if irritation or rash occurs. These may be signs of a serious condition.Not for human body

Keep out of reach of children. If swallowed, get medical help or contact a Poison Control Center right away.

Directions

Spray the product evenly on the surface of the object or finger to be sterilized,without wiping or cleaning.

Other information

STORED IN A COOL,VENTILATED AND DRY PLACE ,USE THIS PRODUCT AS SOON AS POSSIBLE AFTER OPENING THE BOTTLE.

Inactive ingredients

water